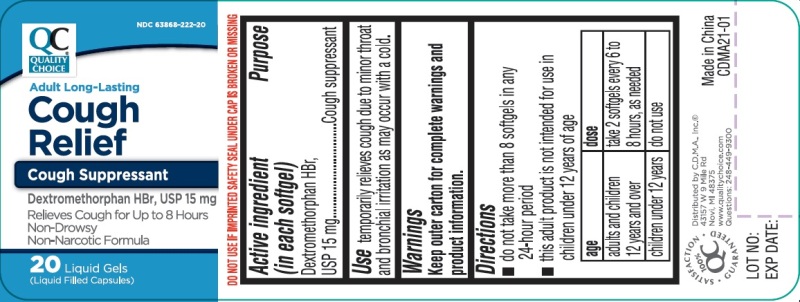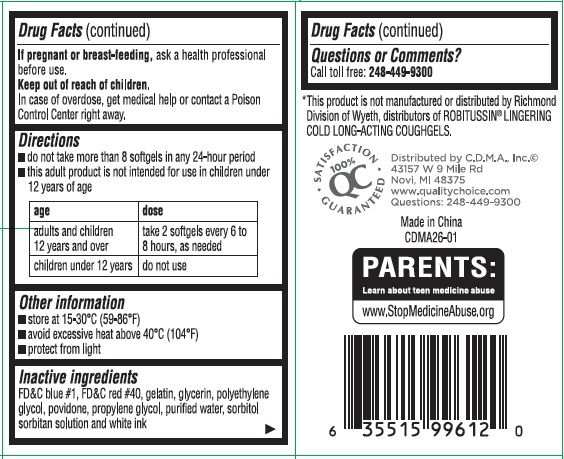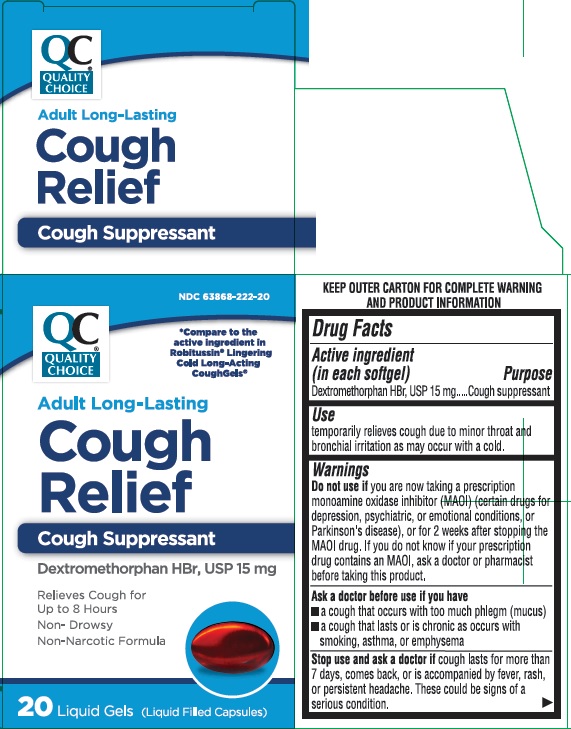 DRUG LABEL: Cough Relief
NDC: 63868-222 | Form: CAPSULE, LIQUID FILLED
Manufacturer: Chain Drug Marketing Association Inc.
Category: otc | Type: HUMAN OTC DRUG LABEL
Date: 20191230

ACTIVE INGREDIENTS: DEXTROMETHORPHAN HYDROBROMIDE 15 mg/1 1
INACTIVE INGREDIENTS: FD&C BLUE NO. 1; FD&C RED NO. 40; GELATIN; GLYCERIN; POLYETHYLENE GLYCOL, UNSPECIFIED; POVIDONE; PROPYLENE GLYCOL; WATER; SORBITOL; SORBITAN

Long-Lasting Cough Relief

Drug Facts

Active ingredient (in each softgel)

Dextromethorphan HBr, USP 15 mg

Purpose

Cough suppressant

Use

temporarily relieves cough due to minor throat and bronchial irritation as may occur with a cold.

Warnings

Do not use if you are now taking a prescription monoamine oxidase inhibitor (MAOI) (certain drugs for depression, psychiatric, or emotional conditions, or Parkinson's disease), or for 2 weeks after stopping the MAOI drug. If you do not know if your prescription drug contains an MAOI, ask a doctor or pharmacist before taking this product.

Ask a doctor before use if you have

- a cough that occurs with too much phlegm (mucus)
- a cough that lasts or is chronic as occurs with smoking, asthma, or emphysema

Stop use and ask a doctor if cough lasts for more than 7 days, comes back, or is accompanied by fever, rash, or persistent headache. These could be signs of a serious condition.

PREGNANCY OR BREAST FEEDING

If pregnant or breast-feeding, ask a health professional before use.

Keep out of reach of children.

In case of overdose, get medical help or contact a Poison Control Center right away.

Directions

- do not take more than 8 softgels in any 24-hour period
- this adult product is not intended for use in children under 12 years of age

age | dose
adults and children 12 years and over | take 2 softgels every 6 to 8 hours, as needed
children under 12 years | do not use

Other information

- store at room temperature 15-30°C (59-86°F)
- avoid excessive heat above 40°C (104°F)
- protect from light

Inactive ingredients

FD&C blue #1, FD&C red #40, gelatin, glycerin, polyethylene glycol, povidone, propylene glycol, purified water, sorbitol sorbitan solution and white edible ink

Questions or comments?

Call toll free: 248-449-9300

PRINCIPAL DISPLAY PANEL

ADULT LONG-LASTING Cough Relief

Dextromethorphan HBr, USP 15 mg 20 Softgels

NDC 63868-222-20

*Compare to the active ingredient in Robitussin® Lingering Cold Long-Acting CoughGels®